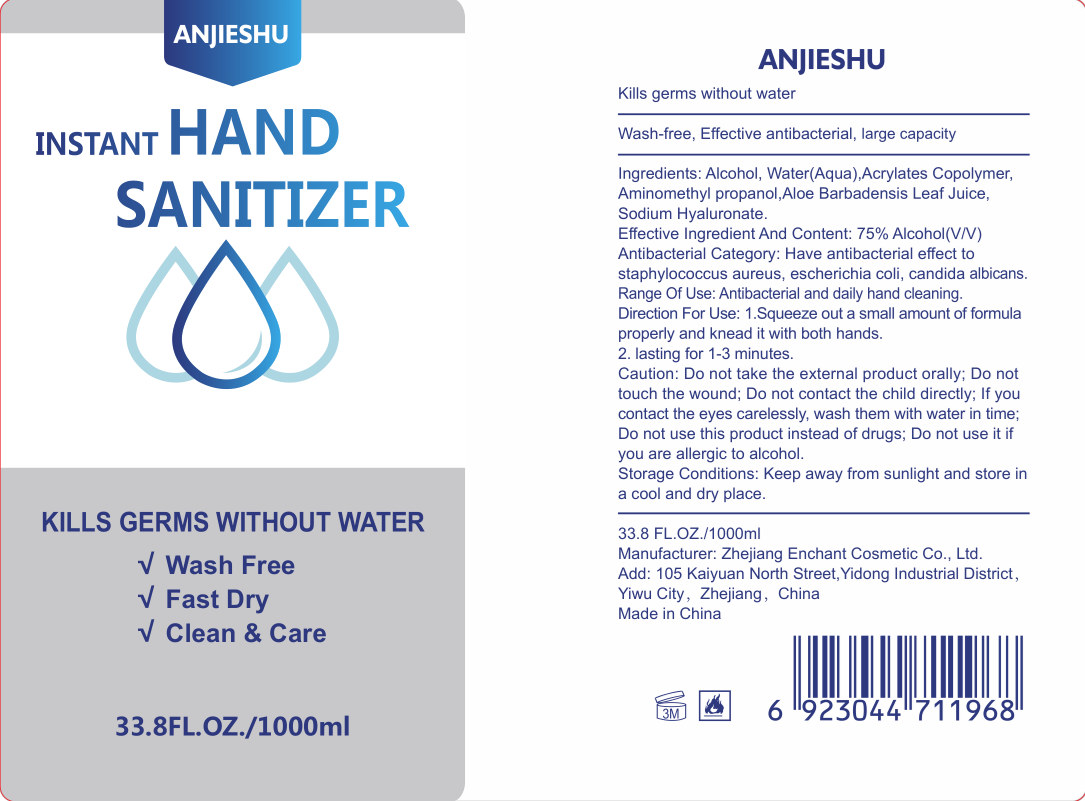 DRUG LABEL: HAND SANITIZER
NDC: 52728-015 | Form: GEL
Manufacturer: Zhejiang Enchant Cosmetic Co., Ltd.
Category: otc | Type: HUMAN OTC DRUG LABEL
Date: 20200429

ACTIVE INGREDIENTS: ALCOHOL 750 mL/1000 mL
INACTIVE INGREDIENTS: HYALURONATE SODIUM; WATER; AMINOMETHYLPROPANOL; BUTYL ACRYLATE/METHYL METHACRYLATE/METHACRYLIC ACID COPOLYMER (18000 MW); ALOE VERA LEAF

DOSAGE AND ADMINISTRATION

Keep away from sunlight and store in a cool and dry place.

INACTIVE INGREDIENT

Water(Aqua)

Acrylates Copolymer

Aminomethyl propanol

Aloe Barbadensis Leaf Juice

Sodium Hyaluronate

INDICATIONS AND USAGE

1. Squeeze out a small amount of formula properly and knead it with both hands.

2. lasting for 1-3 minutes.

ACTIVE INGREDIENT

Alcohol

keep out of reach of children

PURPOSE

Wash Free
Fast Dry
Clean & Care

WARNINGS

Do not take the external product orally; Do not touch the wound; Do not contact the child directly; If you contact the eyes carelessly, wash them with water in time; Do not use this product instead of drugs; Do not use it if you are allergic to alcohol.Storage Conditions: Keep away from sunlight and store in a cool and dry place.